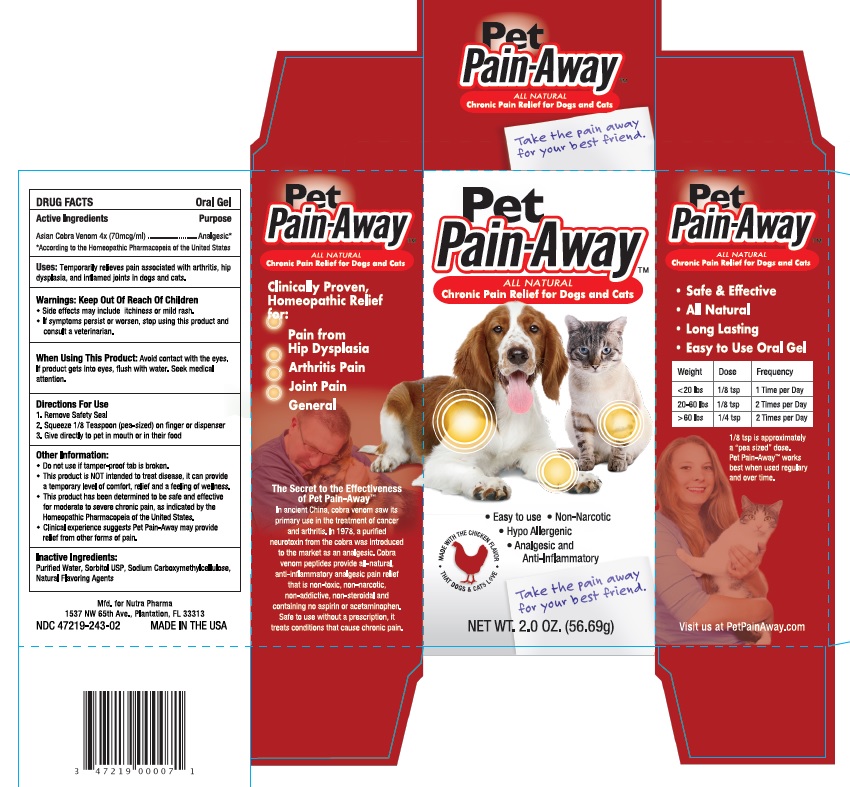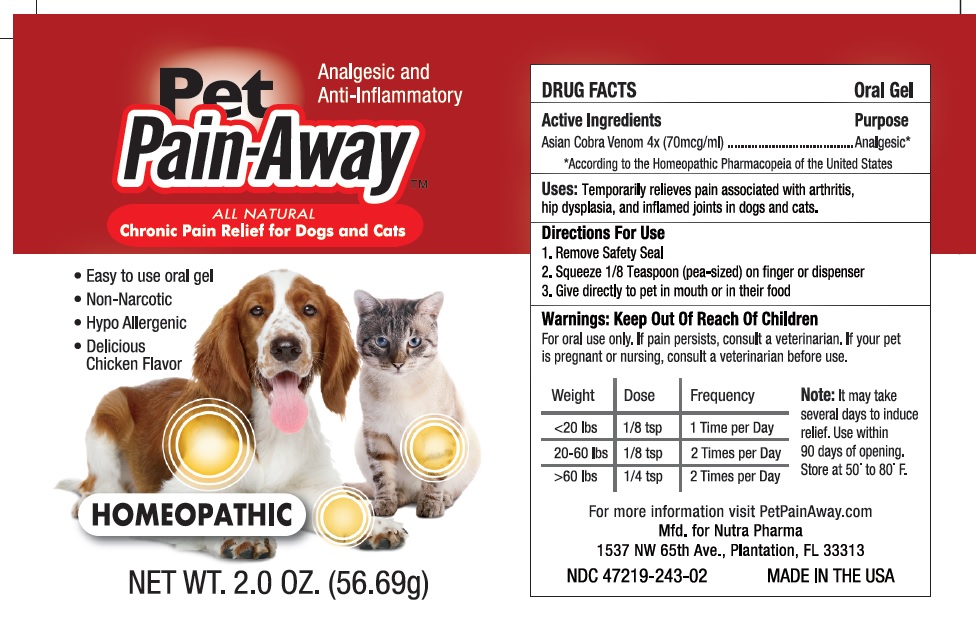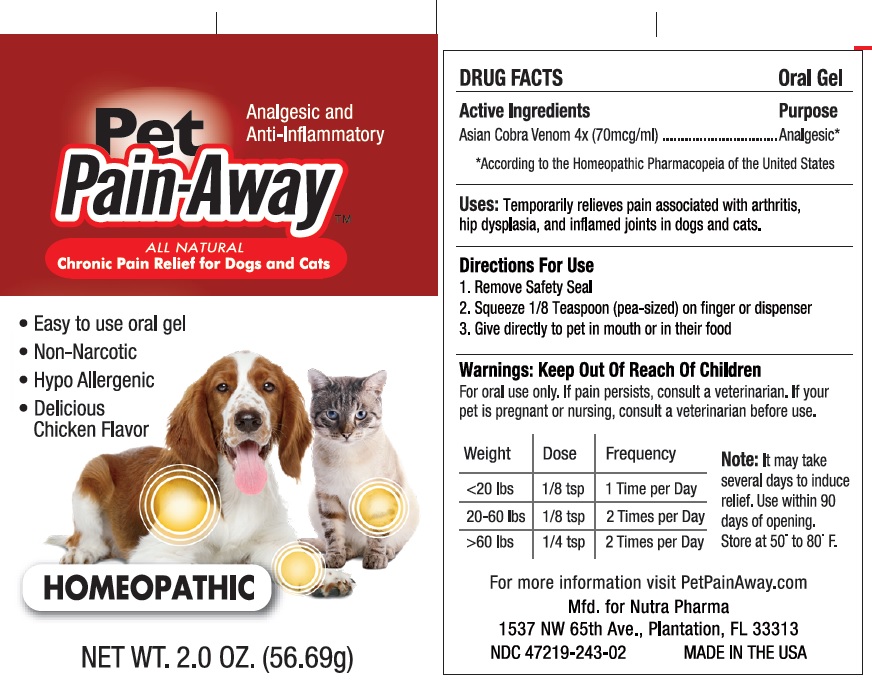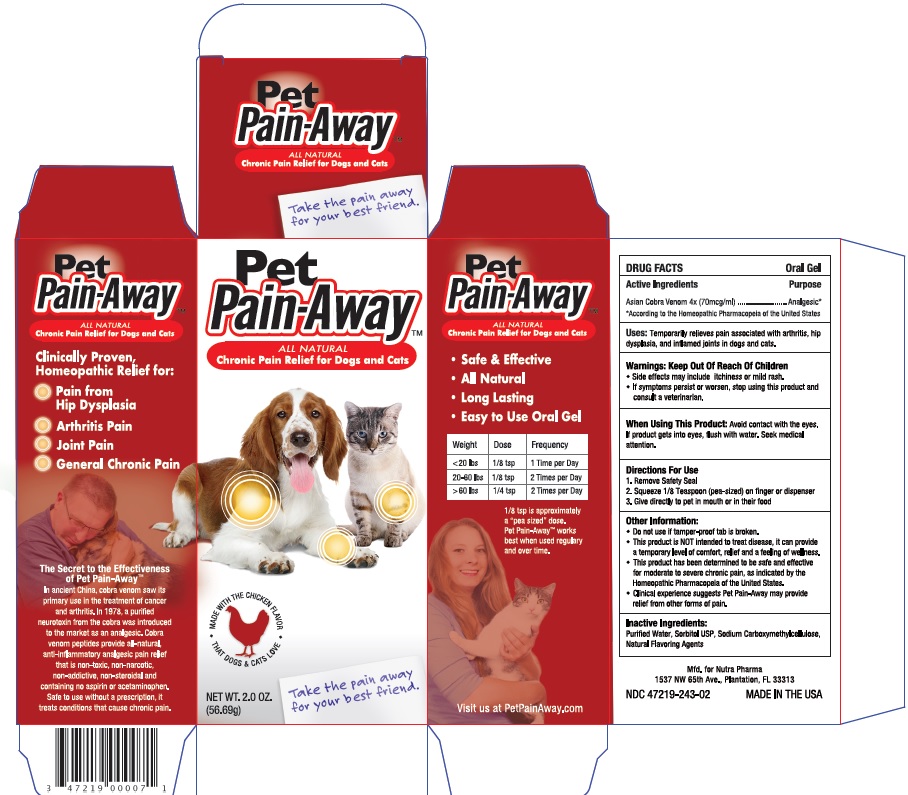 DRUG LABEL: Pet Pain-Away
NDC: 47219-243 | Form: PASTE
Manufacturer: Nutra Pharma Corporation
Category: homeopathic | Type: OTC ANIMAL DRUG LABEL
Date: 20221129

ACTIVE INGREDIENTS: Naja Naja Venom 70 ug/1 mL
INACTIVE INGREDIENTS: WATER; SORBITOL; CARBOXYMETHYLCELLULOSE SODIUM, UNSPECIFIED FORM

Pet Pain-Away™

DRUG FACTS
Oral Gel

Active Ingredients

Asian Cobra Venom 4x (70mcg/ml)

Purpose

Analgesic [According to the Homeopathic Pharmacopeia of the United States]

INFORMATION FOR OWNERS/CAREGIVERS

Uses: Temporarily relieves pain associated with arthritis, hip dysplasia, and inflamed joints in dogs and cats.

Warnings: Keep Out Of Reach Of Children

- Side effects may include itchiness or mild rash.
- If symptoms persist or worsen, stop using this product and consult a veterinarian.

When Using This Product: Avoid contact with the eyes. If product gets into eyes, flush with water. Seek medical attention.

Directions For Use

1. Remove Safety Seal
2. Squeeze 1/8 Teaspoon (pea-sized) on finger or dispenser
3. Give directly to pet in mouth or in their food

Other Information:

- Do not use if tamper-proof tab is broken.
- This product is NOT intended to treat disease, it can provide a temporary level of comfort, relief and a feeling of wellness.
- This product has been determined to be safe and effective for moderate to severe chronic pain, as indicated by the Homeopathic Pharmacopeia of the United States.
- Clinical experience suggests Pet Pain-Away may provide relief from other forms of pain.

Inactive Ingredients:

Purified Water, Sorbitol USP, Sodium Carboxymethylcellulose, Natural Flavoring Agents

Weight | Dose | Frequency
< 20 lbs | 1/8 tsp | 1 Time per Day
20-60 lbs | 1/8 tsp | 2 Times per Day
> 60 lbs | 1/4 tsp | 2 Times per Day

Mfd. for Nutra Pharma

1537 NW 65th Avenue

Plantation, FL 33313

NDC 47219-241-01
MADE IN THE USA